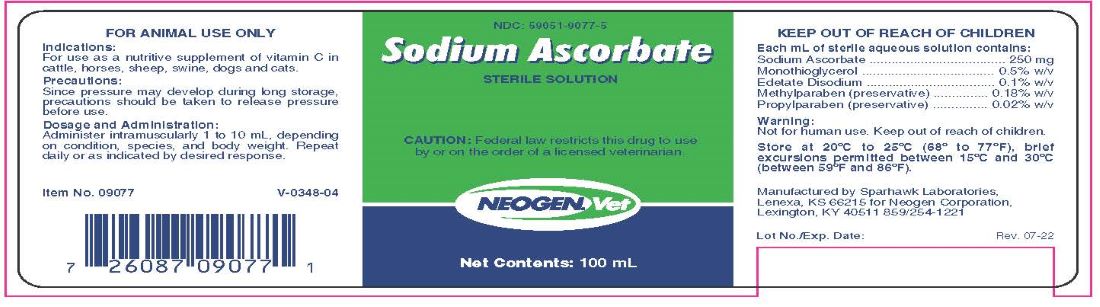 DRUG LABEL: SODIUM ASCORBATE
NDC: 59051-9077 | Form: INJECTION
Manufacturer: Neogen Corporation - Nandino
Category: animal | Type: PRESCRIPTION ANIMAL DRUG LABEL
Date: 20231211

ACTIVE INGREDIENTS: SODIUM ASCORBATE 250 mg/1 mL

Sodium Ascorbate

INDICATIONS AND USAGE

INJECTABLE SOLUTION

CAUTION: Federal law restricts this drug to use by or on the order of a licensed veterinarian.

FOR ANIMAL USE ONLY

KEEP OUT OF REACH OF CHILDREN

INDICATIONS

For use as a nutritive supplement of vitamin C in cattle, horses, sheep, swine, dogs and cats.

PRECAUTIONS

Since pressure may develop on long storage, precautions should be taken to release pressure before use. Storage under refrigeration will reduce possibility of pressure build-up.

DOSAGE AND ADMINISTRATION

Administer intramuscularly 1 to 10 mL, depending on condition, species, and body weight. Repeat daily or as indicated by desired response.

TAKE TIME OBSERVE LABEL DIRECTIONS

COMPOSITION

Each mL of sterile aqueous solution contains:

Sodium Ascorbate . . . . . . . . . . . 250 mg

Monothioglycerol . . . . . . . . . . . 0.5% w/v

Edetate Disodium . . . . . . . . . . 0.1% w/v

Methylparaben (preservative) . . 0.18% w/v

Propylparaben (preservative) . . 0.02% w/v

STORAGE AND HANDLING

Store at 20ºC to 25ºC (68º to 77ºF), brief excursions permitted between 15ºC and 30ºC (between 59ºF and 86ºF).
Protect from light.